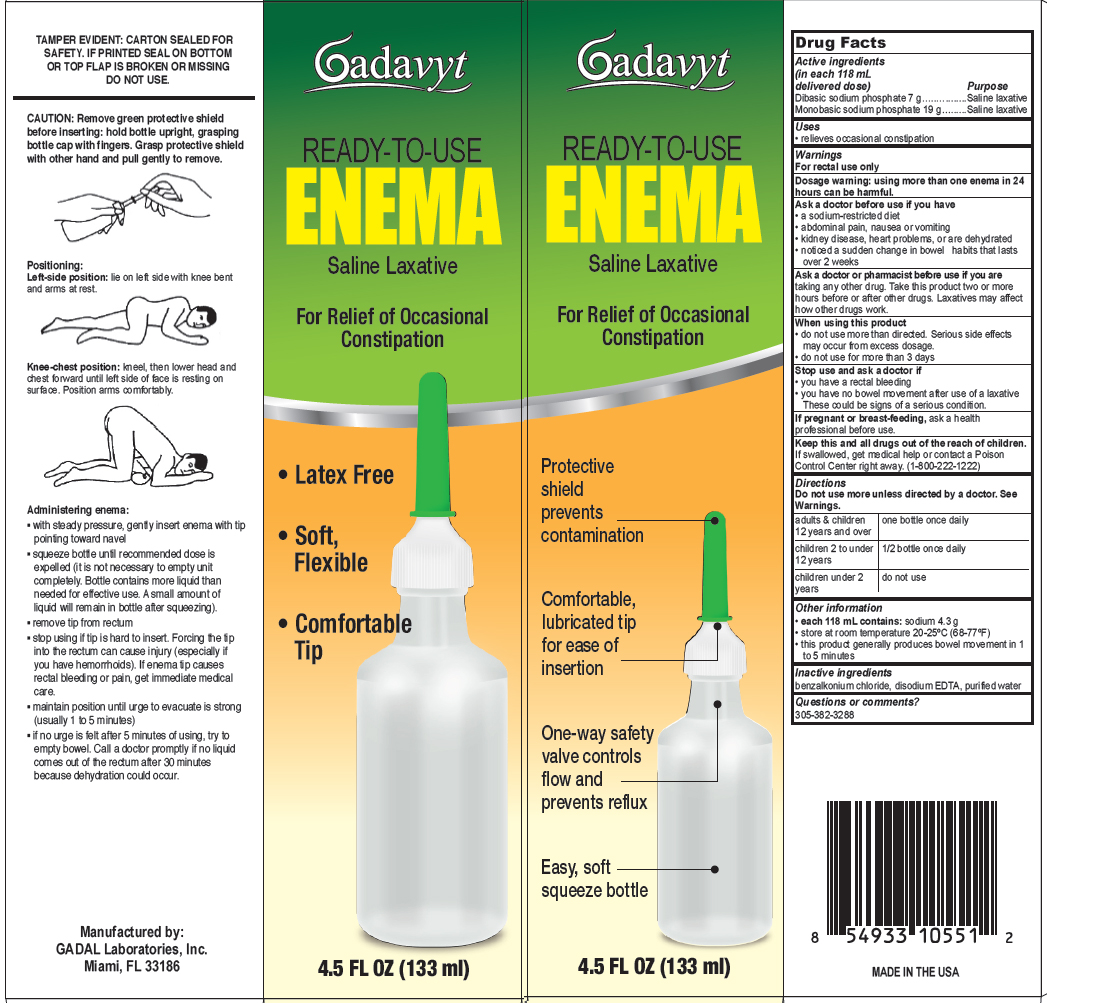 DRUG LABEL: Gadavyt Enema
NDC: 53113-104 | Form: LIQUID
Manufacturer: Gadal Laboratories Inc
Category: otc | Type: HUMAN OTC DRUG LABEL
Date: 20121031

ACTIVE INGREDIENTS: SODIUM PHOSPHATE, DIBASIC 7 g/118 mL; SODIUM PHOSPHATE, MONOBASIC 19 g/118 mL
INACTIVE INGREDIENTS: BENZALKONIUM CHLORIDE; EDETATE DISODIUM; WATER

Drug Facts

Active ingredients (in each 118 mL delivered dose)

Dibasic sodium phosphate 7 g............. Saline Laxative

Monobasic sodium phosphate 19 g......... Saline Laxative

Uses

- relieves occasional constipation

Warnings

For rectal use only

Dosage warning: Using more than one enema in 24 hours can be harmful.

Ask a doctor before use if you have

- a sodium-restricted diet
- abdominal pain, nausea or vomiting
- kidney disease, heart problems, or are dehydrated
- noticed a sudden change in bowel habits that lasts over 2 weeks

Ask a doctor or pharmacist before use if you are

taking any other drug. Take this product two or more hours before or after other drugs. Laxatives may affect how other drugs work.

When using this product

- do not use more than directed. Serious side effects may occur from excess dosage.
- do not use for more than 3 days

Stop use and ask a doctor if

- you have rectal bleeding
- you have no bowel movement after use of a laxative

These could be signs of a serious condition.

If pregnant or breast-feeding,

ask a health professional before use.

Keep out of reach of children.

If swallowed, get medical help or contact a Poison Control Center right away. (1-800-222-1222)

Directions

Do not use more unless directed by a doctor. See Warnings.

adults and children 12 years and over | one bottle once daily
children 2 to under 12 years | 1/2 bottle once daily
children under 2 years | do not use

Other information

- each 118 mL contains: sodium 4.3 g
- store at room temperature 20-25 degrees C (68 -77 degrees F)
- this product generally produces bowel movement in 1 to 5 minutes

Inactive ingredients

benzalkonium chloride, disodium EDTA, purified water

Questions or comments?

305-382-3288